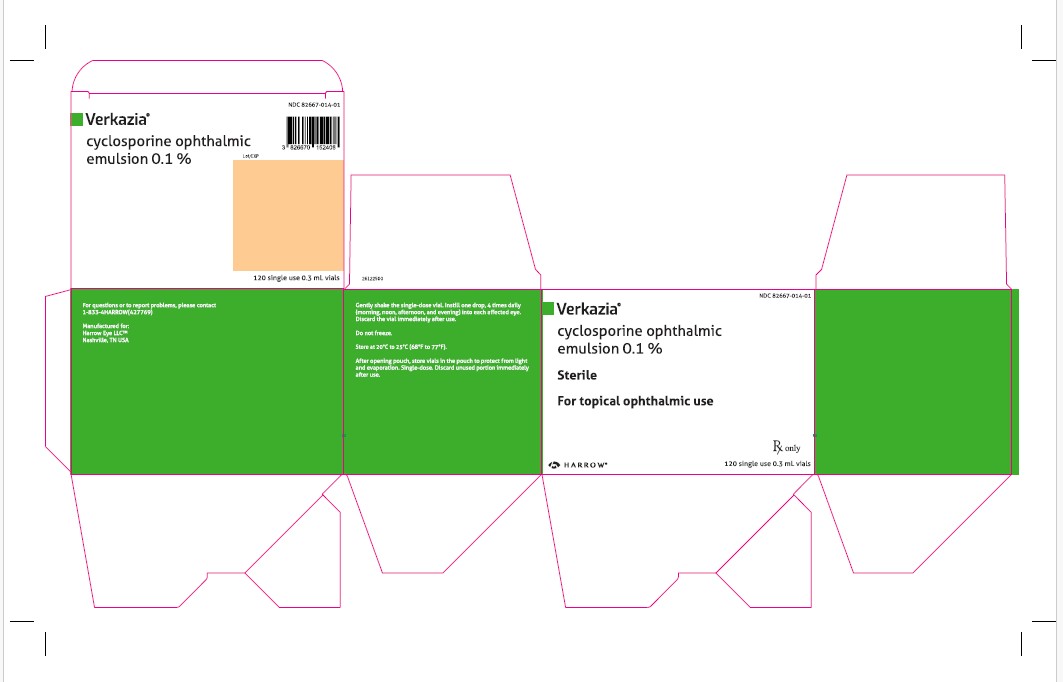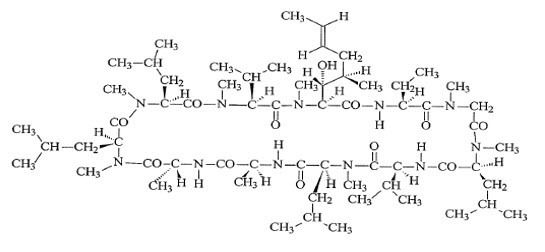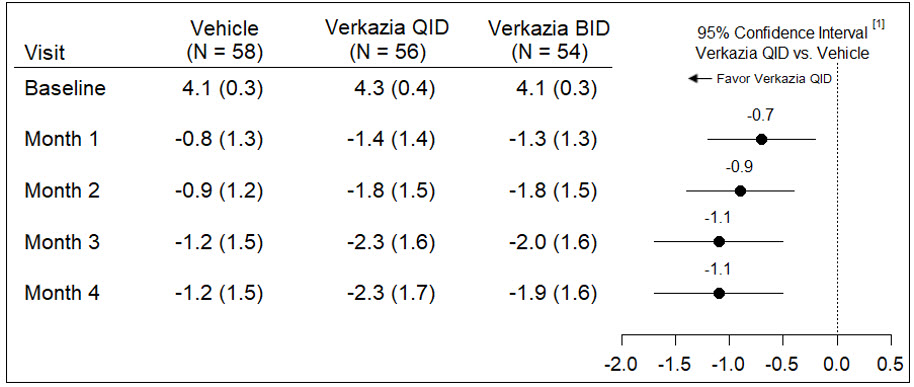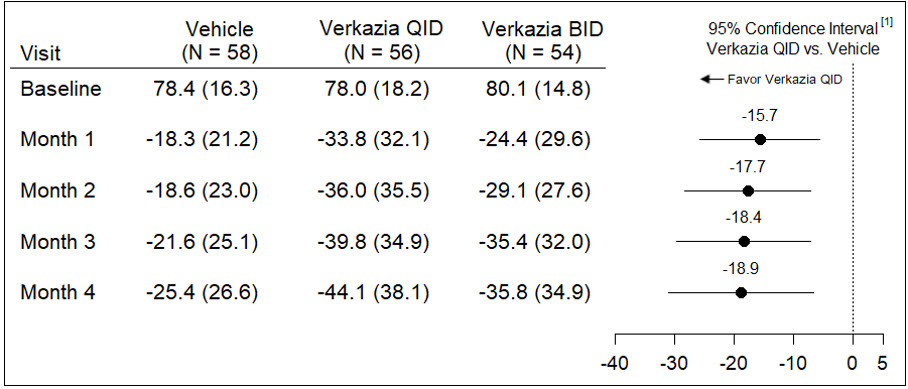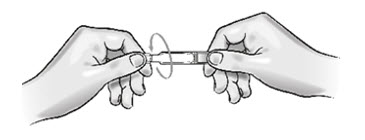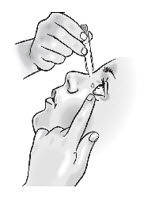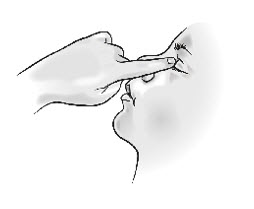 DRUG LABEL: Verkazia
NDC: 82667-014 | Form: EMULSION
Manufacturer: Harrow Eye, LLC
Category: prescription | Type: HUMAN PRESCRIPTION DRUG LABEL
Date: 20260115

ACTIVE INGREDIENTS: CYCLOSPORINE 1 mg/1 mL
INACTIVE INGREDIENTS: TYLOXAPOL; POLOXAMER 188; WATER; SODIUM HYDROXIDE; MEDIUM-CHAIN TRIGLYCERIDES; CETALKONIUM CHLORIDE; GLYCERIN

HIGHLIGHTS OF PRESCRIBING INFORMATION

These highlights do not include all the information needed to use VERKAZIA safely and effectively. See full prescribing information for VERKAZIA.
Verkazia® (cyclosporine ophthalmic emulsion) 0.1%,
for topical ophthalmic use
Initial U.S. Approval: 1983

1 INDICATIONS AND USAGE

Verkazia ophthalmic emulsion is a calcineurin inhibitor immunosuppressant indicated for the treatment of vernal keratoconjunctivitis in children and adults (1)

2 DOSAGE AND ADMINISTRATION

Instill one drop of Verkazia, 4 times daily (morning, noon, afternoon, and evening) in each affected eye (2)

3 DOSAGE FORM AND STRENGTH

Ophthalmic emulsion: 0.1% (1 mg/mL) cyclosporine (3)

4 CONTRAINDICATIONS

None (4)

5 WARNINGS AND PRECAUTIONS

To avoid the potential for eye injury and contamination, advise patient not to touch the vial tip to the eye or other surfaces (5.1)

6 ADVERSE REACTIONS

The most common adverse reactions following the use of Verkazia were eye pain (12%) and eye pruritus (8%) (6.1)

To report SUSPECTED ADVERSE REACTIONS, contact Harrow at 1-833-4HARROW(427769) or FDA at 1-800-FDA-1088 or www.fda.gov/medwatch.

See 17 for PATIENT COUNSELING INFORMATION and FDA‑approved patient labeling.

FULL PRESCRIBING INFORMATION

1 INDICATIONS AND USAGE

Verkazia ophthalmic emulsion is indicated for the treatment of vernal keratoconjunctivitis (VKC) in children and adults.

2 DOSAGE AND ADMINISTRATION

2.1 General Dosing Information

Gently shake the single-dose vial several times to obtain a uniform, white, opaque emulsion before use.

Contact lenses should be removed before applying Verkazia and may be reinserted
15 minutes after administration.

If a dose is missed, treatment should be continued as normal, at the next scheduled administration.

If more than one topical ophthalmic product is being used, administer the eye drops at least 10 minutes apart to avoid diluting products. Administer Verkazia 10 minutes prior to using any eye ointment, gel or other viscous eye drops.

Discard the vial immediately after use.

2.2 Recommended Dosage and Dose Administration

Instill one drop of Verkazia, 4 times daily (morning, noon, afternoon, and evening) into each affected eye.

Treatment can be discontinued after signs and symptoms are resolved and can be reinitiated if there is a recurrence.

3 DOSAGE FORM AND STRENGTH

Ophthalmic emulsion: 0.1% (1 mg/mL) cyclosporine

4 CONTRAINDICATIONS

None

5 WARNINGS AND PRECAUTIONS

5.1 Potential for Eye Injury and Contamination

To avoid the potential for eye injury or contamination, advise patients not to touch the vial tip to the eye or other surfaces.

6 ADVERSE REACTIONS

6.1 Clinical Trials Experience

Since clinical trials are conducted under widely varying conditions, adverse reaction rates observed in the clinical trials of a drug cannot be directly compared to rates in the clinical trials of another drug and may not reflect the rates observed in practice.

In the VEKTIS study, a multicenter, randomized, double-masked, placebo‑controlled trial, a total of 57 patients received Verkazia dosed four times a day (QID) for 4 months. Forty-two (42) patients received Verkazia in an 8 month extension, safety follow-up of the VEKTIS study. In the NOVATIVE study, a multicenter, randomized, double-masked, placebo‑controlled trial, 39 patients received Verkazia 1 mg/mL dosed QID for one month. A total of 53 patients received Verkazia 1 mg/mL QID during a 3-month safety follow‑up. The majority of the treated patients were male (79%). The most common adverse reactions reported in greater than 5% of patients were eye pain (12%) and eye pruritus (8%) which were usually transitory and occurred during instillation (Table 1).

Table 1: Adverse Reactions Reported in ≥ 1% of Patients Receiving Verkazia

 | (N=135)
Eye Disorders
Eye paina | 12%
Eye pruritusb | 8%
Ocular discomfortc | 6%
Visual acuity reduced | 5%
Ocular hyperemia | 4%
Systemic
Cough | 5%
Headache | 4%
Upper respiratory tract infection | 2%
aIncluding eye pain and instillation site pain
bIncluding eye pruritus and instillation site pruritus
cIncluding foreign body sensation and ocular discomfort

8 USE IN SPECIFIC POPULATIONS

8.1 Pregnancy

Risk Summary

There are no adequate and well-controlled studies of Verkazia administration in pregnant women to inform a drug-associated risk. Oral administration of cyclosporine to pregnant rats or rabbits did not produce teratogenicity at clinically relevant doses [see Data].

Data

Animal Data

Oral administration of cyclosporine oral solution (USP) to pregnant rats or rabbits was teratogenic at maternally toxic doses of 30 mg/kg/day in rats and 100 mg/kg/day in rabbits, as indicated by increased pre- and postnatal mortality, reduced fetal weight and skeletal retardations. These doses (normalized to body weight) were approximately 320 and 2150 times higher than the daily maximum recommended human ophthalmic dose (MRHOD) of 0.015 mg/kg/day, respectively.

No adverse embryofetal effects were observed in rats or rabbits receiving cyclosporine during organogenesis at oral doses up to 17 mg/kg/day or 30 mg/kg/day, respectively (approximately 185 and 650 times higher than the MRHOD, respectively).

An oral dose of 45 mg/kg/day cyclosporine (approximately 485 times higher than MRHOD) administered to rats from Day 15 of pregnancy until Day 21 postpartum produced maternal toxicity and an increase in postnatal mortality in offspring. No adverse effects in mothers or offspring were observed at oral doses of up to
15 mg/kg/day (160 times greater than MRHOD).

8.2 Lactation

Risk Summary

There is no information regarding the presence of cyclosporine in human milk following topical administration or on the effect of Verkazia on the breastfed infants and milk production. Administration of oral cyclosporine to rats during lactation did not produce adverse effects in offspring at clinically relevant doses [see Pregnancy (8.1)] . The development and health benefits of breastfeeding should be considered along with the mother’s clinical need for Verkazia and any potential adverse effects on the breast-fed child from cyclosporine.

8.3 Females and Males of Reproductive Potential

Infertility

There are no data on the effects of Verkazia on human fertility. No impairment of fertility has been reported in animals receiving intravenous cyclosporine [see Impairment of Fertility (13.1) ].

8.4 Pediatric Use

Verkazia’s safety and effectiveness has been established in patients from 4 through 18 years of age.

8.5 Geriatric Use

The safety and effectiveness of Verkazia have not been studied in geriatric patients.

11 DESCRIPTION

Verkazia (cyclosporine ophthalmic emulsion) 0.1% contains a topical calcineurin inhibitor immunosuppressant. Cyclosporine is a white or almost white powder. Cyclosporine’s chemical name is Cyclo[[(E)-(2 S,3 R,4 R)-3-hydroxy-4-methyl-2-(methylamino)-6-octenoyl]-L-2-aminobutyryl- N-methylglycyl- N-methyl-L-leucyl-L-valyl- N-methyl-L-leucyl-L-alanyl-D-alanyl- N-methyl-L-leucyl- N-methyl-L-leucyl- N-methyl-L-valyl] and it has the following structure:

Structural Formula

Formula: C62H111N11O12Mol. Wt.: 1202.61

Verkazia ophthalmic emulsion is a sterile, unpreserved topical emulsion. It appears as a milky-white homogeneous emulsion. It has an osmolality of approximately 265 mOsmol/kg and a pH of 5-7. Each mL of Verkazia ophthalmic emulsion contains: Active: Cyclosporine 1 mg/mL. Inactives: Cetalkonium chloride, Glycerol, Medium-chain triglycerides, Poloxamer 188, Sodium Hydroxide to adjust pH, Tyloxapol and Water for Injection.

12 CLINICAL PHARMACOLOGY

12.1 Mechanism of Action

Cyclosporine is a calcineurin inhibitor immunosuppressant agent when administered systemically. Following ocular administration, cyclosporine is thought to act by blocking the release of pro-inflammatory cytokines such as IL-2. The exact mechanism of action in the treatment of VKC is not known.

12.3 Pharmacokinetics

Blood concentrations of cyclosporine were measured in 55 patients administered 1 drop of Verkazia 4 times daily in the VEKTIS Study. Blood samples were collected before administration and after 2, 4, and 12 months of administration of Verkazia. Among those patients that had quantifiable levels of cyclosporine during the study, the maximum blood level of cyclosporine was 0.67 ng/mL.

13 NONCLINICAL TOXICOLOGY

13.1 Carcinogenesis, Mutagenesis, Impairment of Fertility

Carcinogenesis

Systemic carcinogenicity studies were carried out in male and female mice and rats. In the 78-week oral (diet) mouse study, at doses of 1, 4, and 16 mg/kg/day, evidence of a statistically significant trend was found for lymphocytic lymphomas in females, and the incidence of hepatocellular carcinomas in mid-dose males significantly exceeded the control value. The low dose in mice is approximately 5 times greater than MRHOD.

In the 24-month oral (diet) rat study, conducted at 0.5, 2, and 8 mg/kg/day, pancreatic islet cell adenomas significantly exceeded the control rate in the low dose level. The hepatocellular carcinomas and pancreatic islet cell adenomas were not dose related. The low dose in rats is approximately 5 times greater than MRHOD.

Mutagenesis

In genetic toxicity tests, cyclosporine has not been found to be mutagenic/genotoxic in the Ames Test, the V79-HGPRT Test, the micronucleus test in mice and Chinese hamsters, the chromosome-aberration tests in Chinese hamster bone-marrow, the mouse dominant lethal assay, and the DNA-repair test in sperm from treated mice. Cyclosporine was positive in an in vitro sister chromatid exchange (SCE) assay using human lymphocytes.

Impairment of Fertility

Oral administration of cyclosporine to rats for 12 weeks (male) and 2 weeks (female) prior to mating produced no adverse effects on fertility at doses up to 15 mg/kg/day
(160 times higher than MRHOD).

14 CLINICAL STUDIES

The safety and efficacy of Verkazia for the treatment of VKC was evaluated in two randomized, multi-center, double-masked, vehicle-controlled, clinical trials (VEKTIS Study NCT01751126 and NOVATIVE Study NCT00328653).

In the VEKTIS study, patients with severe VKC were randomized to four times daily of Verkazia 1 mg/mL or two times daily (BID) of Verkazia 1 mg/mL and vehicle group for the first 4 months (Period 1). Similarly, in the NOVATIVE study, patients with moderate to severe VKC were randomized to QID of Verkazia 1 mg/mL or QID of cyclosporine ophthalmic emulsion 0.5 mg/mL and vehicle group for the first 1 month (Period 1). In both studies, patients randomized to the vehicle group were switched to Verkazia (QID or BID) from Month 4 to Month 12 in VEKTIS Study and to cyclosporine ophthalmic emulsion 0.5 mg/mL QID or 1 mg/mL from Month 1 to Month 4 in NOVATIVE Study (Period 2).

A total of 168 and 118 patients were enrolled in the VEKTIS and NOVATIVE studies for the efficacy analyses, respectively. Patients’ age ranged from 4 through 17 years (mean age 9 years) in VEKTIS and 4 through 21 years (mean age 9 years) in NOVATIVE, with most patients being between 4 and 11 years of age (76% in VEKTIS and 80% in NOVATIVE) and male (79% in VEKTIS and 81% in NOVATIVE). Most of the patients had both limbal and tarsal forms of VKC (65% in VEKTIS and 74% in NOVATIVE). In both studies, patients had experienced VKC for a mean of 3 years prior to enrollment and all patients had a history of at least one recurrence of VKC in the year prior to study entry.

In the VEKTIS study, key efficacy evaluation was based on the change in corneal fluorescein staining (CFS) score and in itching score over 4 months. The results at each month are presented in Table 2 for the CFS score and in Table 3 for the Itching score.

Table 2: Efficacy Results of the Mean Change in Keratitis Score from Baseline at Each Visit (Full Analysis Set)

[1]Treatment differences (numbers in the middle of the horizontal lines) and 95% confidence intervals (horizontal lines) are based on ANCOVA model including baseline CFS score and the proportion of time potentially spent in taking study medication during the VKC season as covariate. For subjects that received rescue therapy during the study, all post-rescue data were imputed by the last available data observed prior to rescue initiation.

Note 1: CFS score was measured at each month using a 5-point scale (0 = no stain, and 5 = more stain).

Note 2: The Full Analysis Set included all randomized subjects that received at least one drop of study medication.

Table 3: Efficacy Results of the Mean Change in Itching Score from Baseline at Each Visit (Full Analysis Set)

[1]Treatment differences (numbers in the middle of the horizontal lines) and 95% confidence intervals (horizontal lines) are based on ANCOVA model including baseline Itching score and the proportion of time potentially spent in taking study medication as covariate. For subjects that received rescue therapy during the study, all post-rescue data were imputed by the last available data observed prior to rescue initiation.

Note 1: Itching score at each visit was measured using a Visual Analogue Scale (0 = no itch to 100 = maximal itch).

Analyses of the CFS score and Itching score at Month 1 of the efficacy evaluation period in the NOVATIVE Study also provided supporting evidence.

16 HOW SUPPLIED/STORAGE AND HANDLING

Verkazia (cyclosporine ophthalmic emulsion) 0.1% is packaged in low-density polyethylene single-dose vials. Each vial contains 0.3 mL fill; 5 vials are packaged in an aluminum pouch; 24 pouches are packaged in a box of 120 vials.

The entire contents of each box of 120 vials must be dispensed intact.

120 Single-Dose Vials 0.3 mL each — NDC 82667-014-01

Storage: Do not freeze Verkazia. Store at 20°C to 25°C (68°F to 77°F). After opening the aluminum pouch, the single-dose vial should be kept in the pouch to protect from light and avoid evaporation. Any opened individual single-dose vial with any remaining emulsion should be discarded immediately after use.

17 PATIENT COUNSELING INFORMATION

Advise the patient to read the FDA-approved patient labeling (Instructions for Use).

Handling the Vial

Advise patients to not allow the tip of the vial to touch the eye or any surface, as this may contaminate the emulsion. Advise patients to not touch the vial tip to their eye to avoid the potential for injury to the eye [see Warnings and Precautions (5.1)].

Use with Contact Lenses

Advise patients that contact lenses should be removed before administering Verkazia and to wait at least 15 minutes after instillation of the dose before reinserting the contact lenses [see Dosage and Administration (2.1)] .

Administration

Advise patients that the emulsion from one individual single-dose vial is to be used immediately after opening for administration to one or both eyes, and the remaining contents should be discarded immediately after administration [see Dosage and Administration (2) ].

Missed Dose

If a dose is missed, Verkazia should be continued as normal at the next dose as planned. [see Dosage and Administration (2.1)] .

Manufactured for:
Harrow Eye LLC™
Nashville, TN USA

INSTRUCTIONS FOR USE

Verkazia® [ver ka' zee ah]
(cyclosporine ophthalmic emulsion, 0.1%)
for topical ophthalmic use

Read this Instructions for Use before you start using Verkazia and each time you get a refill. There may be new information. This leaflet does not take the place of talking to your healthcare provider about your medical condition or your treatment.

Important Information You Need to Know Before Using Verkazia

- Verkazia is for use in the eye.
- Verkazia is supplied as 5 single-dose vials packaged in a foil pouch.
- If you are using any other eye drops, use each eye drop at least 10 minutes apart from each other, including Verkazia.
- If you are using any eye ointment, gel or other thicker in consistency (viscous) eye drops, use Verkazia 10 minutes before using them.
- Do notlet the tip of the Verkazia vial touch your eye or any other surfaces to avoid contamination or injury to your eye.
- Adults should help children when starting treatment. Adults should continue to help until the child is able to properly use Verkazia alone. Use 1 drop of Verkazia in the affected eye or eyes, 4 times a day (morning, noon, afternoon and evening). There is enough medicine in one vial to use in both eyes. Throw away (discard) the vial immediately after use.
- If you forget to use Verkazia, skip that dose and continue with the next dose as planned.
- Contact lenses should be taken out before using Verkazia and wait at least 15 minutes after giving the dose before putting the contact lenses back into your eyes.
- Do notuse Verkazia after the expiration date (EXP) appearing on the outer carton, pouch and single-dose vial. The expiration date is the last day of that month.

Using Verkazia

Follow the instructions (Step 1to Step 12) each time you use Verkazia. If there is anything that you do not understand, ask your healthcare provider.

Step 1. Wash your hands.

Step 2. Open the aluminum pouch, which contains 5 single-dose vials.

Step 3. Take 1 vial from the aluminum pouch. Leave the remaining vials in the pouch.

Step 4. Gently shake the vial.

Step 5. Twist off the cap (see Figure A).

Figure A

Step 6. Pull down your lower eyelid (see Figure B).

Figure B

Step 7. Tilt your head back and look up.

Step 8. Gently squeeze 1 drop of the medicine onto your eye. Make sure that the tip of the vial does not touch your eye. If a drop misses your eye, try again.

Step 9. Blink a few times so that the medicine spreads across your eye.

Step 10. After using Verkazia, press the corner of your eye closest to your nose and gently close the eyelid for 2 minutes (see Figure C).

Figure C

Step 11. If you need to use drops in both eyes, repeat Steps 6to 10for your other eye. There is enough medicine in one single-dose vial to use in both eyes.

Step 12. Throw away the vial with any remaining medicine after use.

Storing Verkazia

- Store Verkazia at room temperature between 68°F to 77°F (20°C to 25°C).
- Do not freeze.
- After opening the pouch, keep vials in the pouch to protect from light and evaporation.

Throwing away Verkazia

- Any open vial with any medicine left over should be thrown out right after use.

Talk with your healthcare provider if you want more information about Verkazia.

Manufactured for:
Harrow Eye, LLCTM
Nashville, TN USA

This Instructions for Use has been approved by the U.S. Food and Drug Administration.

Approved: June 2021

PRINCIPAL DISPLAY PANEL

NDC 82667-014-01
Verkazia®
cyclosporine ophthalmic

emulsion 0.1%

Sterile

For topical ophthalmic use

Rx only

Harrow Eye, LLCTM

120 single use 0.3 mL vials